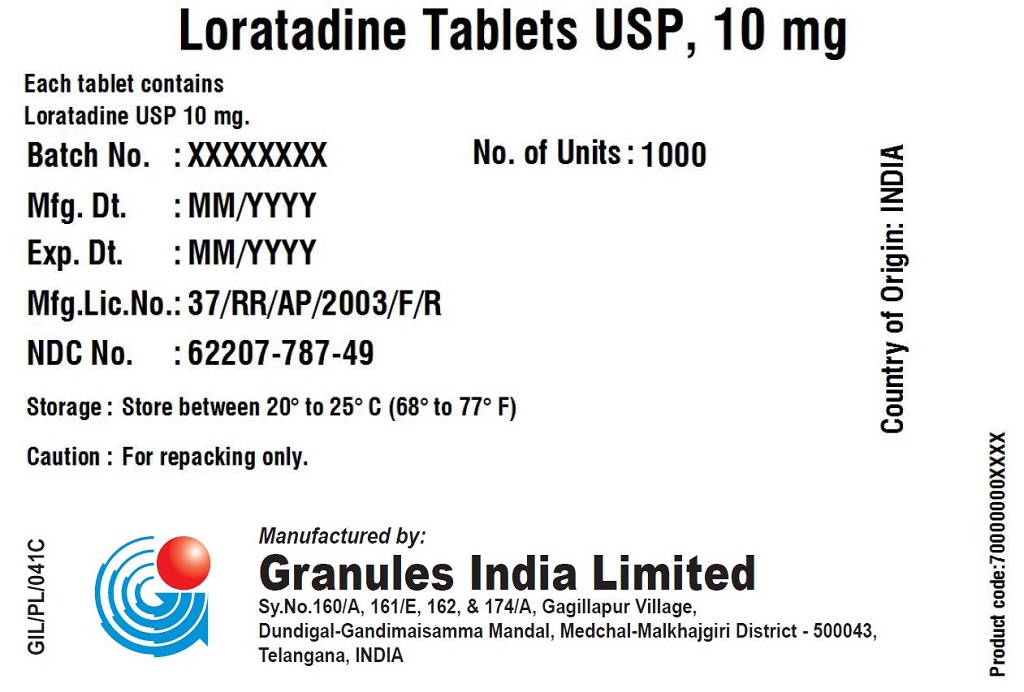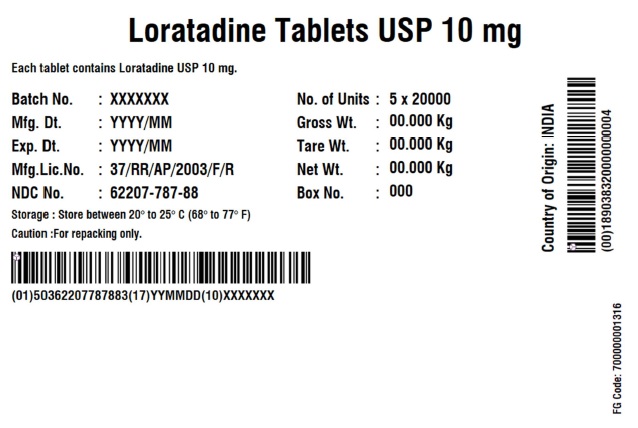 DRUG LABEL: Loratadine
NDC: 62207-787 | Form: TABLET
Manufacturer: Granules India Limited
Category: otc | Type: HUMAN OTC DRUG LABEL
Date: 20250801

ACTIVE INGREDIENTS: LORATADINE 10 mg/1 1
INACTIVE INGREDIENTS: MAGNESIUM STEARATE; SODIUM STARCH GLYCOLATE TYPE A POTATO; LACTOSE MONOHYDRATE; STARCH, CORN

Loratadine Tablets, 10 mg

ACTIVE INGREDIENT

Loratadine 10 mg

PURPOSE

Antihistamine

USES

temporarily relieves these symptoms due to hay fever or other upper respiratory allergies:

- runny nose
- itchy, watery eyes
- sneezing
- itching of the nose or throat

WARNINGS

Do not use if you have ever had an allergic reaction to this product or any of its ingredients

ASK A DOCTOR BEFORE USE IF

you have liver or kidney disease. Your doctor should determine if you need a different dose.

WHEN USING THIS PRODUCT

do not take more than directed. Taking more than directed may cause drowsiness.

STOP USE AND ASK DOCTOR IF

an allergic reaction to this product occurs. Seek medical help right away.

IF PREGNANT OR BREAST-FEEDING

ask a health professional before use.

KEEP OUT OF REACH OF CHILDREN

In case of overdose, get medical help or contact a Poison Control Center right away.

DIRECTIONS

adults and children 6 years and over | 1 tablet daily; not more than 1 tablet in 24 hours
children under 6 years of age | ask a doctor
consumers with liver or kidney disease | ask a doctor

OTHER INFORMATION

- Tamper-evident: do not use if foil seal under cap, printed with "SEALED for YOUR PROTECTION" is missing, open or broken
- store between 20° to 25°C (68° to 77°F)

INACTIVE INGREDIENTS

Lactose monohydrate, magnesium stearate, sodium starch glycolate and starch maize pregelatinized

QUESTIONS OR COMMENTS

Contact 1-877-770-3183 Mon-Fri 9:00 AM to 4:30 PM EST